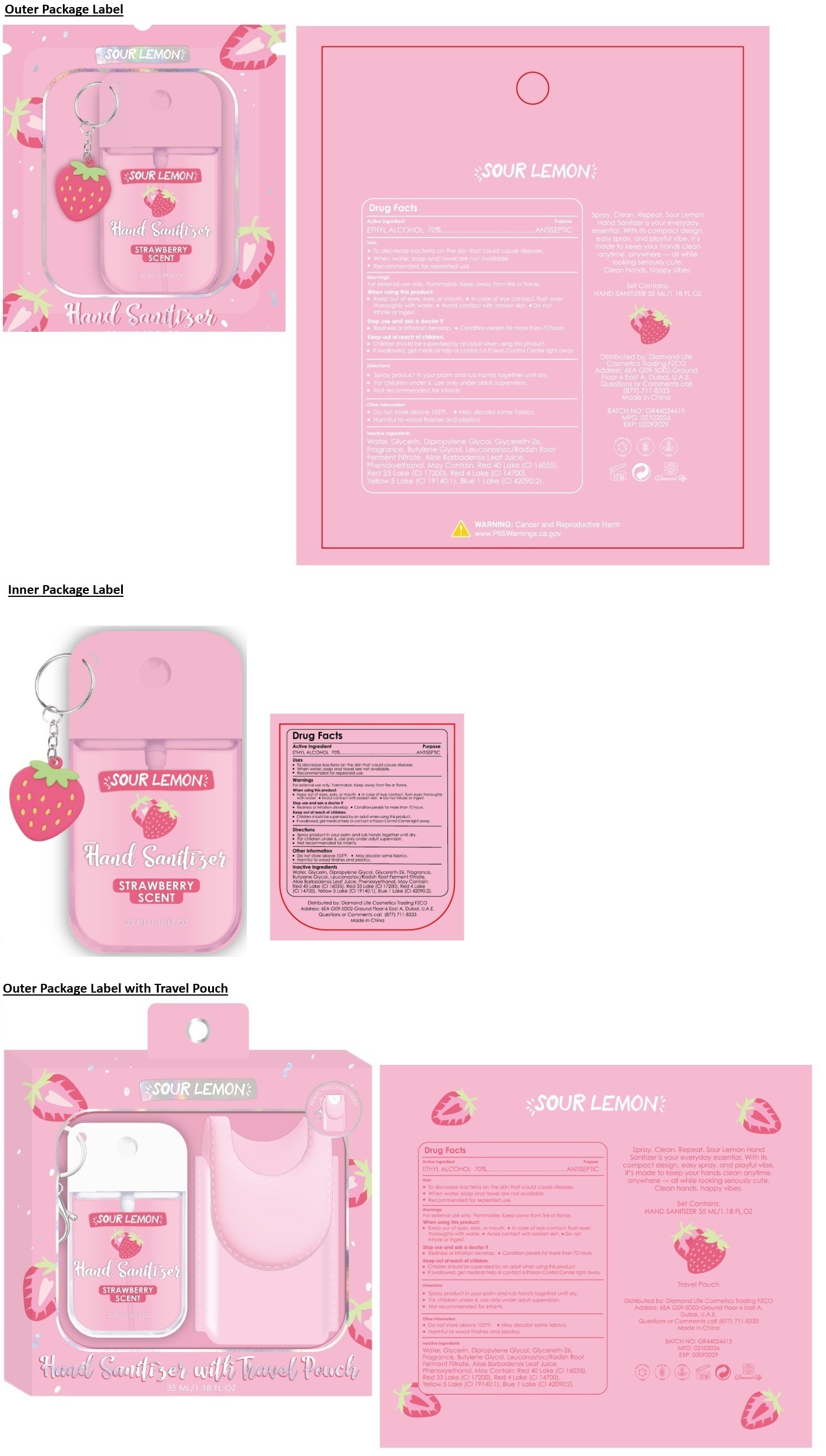 DRUG LABEL: SOUR LEMON Hand Sanitizer STRAWBERRY SCENT
NDC: 87247-420 | Form: SPRAY
Manufacturer: Diamond Life Cosmetics Trading FZCO
Category: otc | Type: HUMAN OTC DRUG LABEL
Date: 20260219

ACTIVE INGREDIENTS: ALCOHOL 70 mL/100 mL
INACTIVE INGREDIENTS: WATER; GLYCERIN; DIPROPYLENE GLYCOL; GLYCERETH-26; BUTYLENE GLYCOL; LEUCONOSTOC/RADISH ROOT FERMENT FILTRATE; ALOE VERA LEAF JUICE; PHENOXYETHANOL; FD&C RED NO. 40 ALUMINUM LAKE; D&C RED NO. 33; FD&C RED NO. 4; FD&C YELLOW NO. 5 ALUMINUM LAKE; FD&C BLUE NO. 1 ALUMINUM LAKE

SOUR LEMON Hand Sanitizer STRAWBERRY SCENT

Active Ingredient

ETHYL ALCOHOL 70%

Purpose

ANTISEPTIC

Uses

• To decrease bacteria on the skin that could cause disease.
• When water, soap and towel are not available.
• Recommended for repeated use.

Warnings

For external use only. Flammable. Keep away from fire or flame.

When using this product:
• Keep out of eyes, ears, or mouth. • In case of eye contact, flush eyes thoroughly with water. • Avoid contact with broken skin. • Do not inhale or ingest.

Stop use and ask a doctor if
• Redness or irritation develop. • Condition persists for more than 72 hours.

Keep out of reach of children.
• Children should be supervised by an adult when using this product.
• If swallowed, get medical help or contact a Poison Control Center right away.

Directions

• Spray product in your palm and rub hands together until dry.
• For children under 6, use only under adult supervision.
• Not recommended for infants.

Other Information

• Do not store above 105°F. • May discolor some fabrics.
• Harmful to wood finishes and plastics.

Inactive Ingredients

Water, Glycerin, Dipropylene Glycol, Glycereth-26, Fragrance, Butylene Glycol, Leuconostoc/Radish Root Ferment Filtrate, Aloe Barbadensis Leaf Juice, Phenoxyethanol. May Contain: Red 40 Lake (CI 16035), Red 33 Lake (CI 17200), Red 4 Lake (CI 14700), Yellow 5 Lake (CI 19140:1), Blue 1 Lake (CI 42090:2).

TRAVEL POUCH INCLUDED

Hand Sanitizer with Travel Pouch

Spray. Clean. Repeat. Sour Lemon Hand Sanitizer is your everyday essential. With its compact design, easy spray, and playful vibe, it's made to keep your hands clean anytime, anywhere - all while looking seriously cute. Clean hands, happy vibes.

Set Contains:
HAND SANITIZER 35 ML/1.18 FL.OZ
Travel Pouch

Distributed by: Diamond Life Cosmetics Trading FZCO
Address: 6EA G09-SD02-Ground Floor-6 East A, Dubai, U.A.E
Questions or Comments call (877) 711-8333
Made in China

PHTHALATES FREE

GLUTEN FREE

PARABEN FREE

WARNING: Cancer and Reproductive Harm
www.P65Warnings.ca.gov